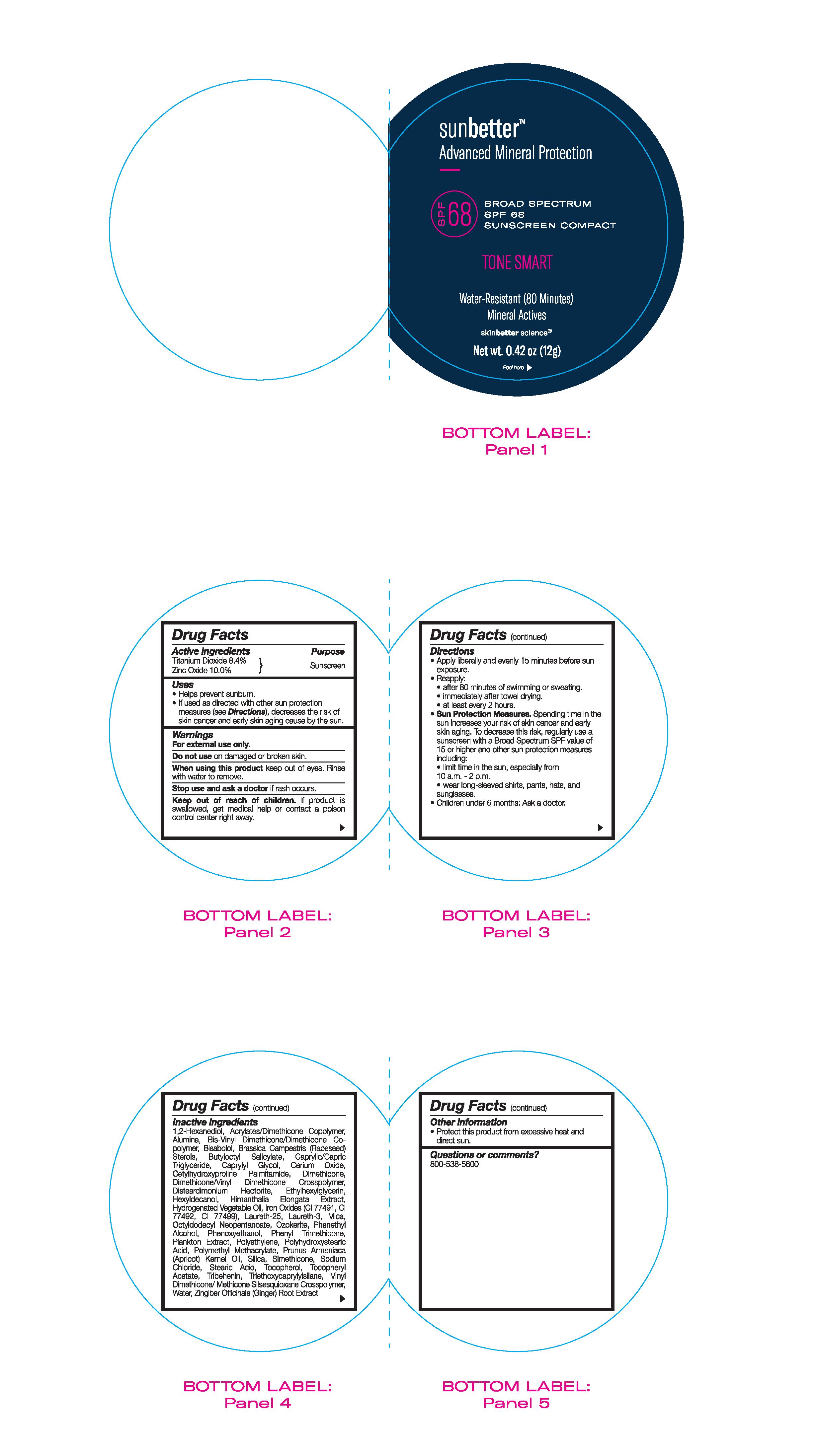 DRUG LABEL: sunbetter Broad Spectrum SPF 68 Sunscreen Compact Tone Smart
NDC: 73291-0001 | Form: STICK
Manufacturer: SKINBETTER SCIENCE LLC
Category: otc | Type: HUMAN OTC DRUG LABEL
Date: 20250106

ACTIVE INGREDIENTS: ZINC OXIDE 100 mg/1 g; TITANIUM DIOXIDE 84 mg/1 g
INACTIVE INGREDIENTS: CORN OIL; PHENYL TRIMETHICONE; HEXYLDECANOL; CETYLHYDROXYPROLINE PALMITAMIDE; ETHYLHEXYLGLYCERIN; HIMANTHALIA ELONGATA; PHENYLETHYL ALCOHOL; OCTYLDODECYL NEOPENTANOATE; TRIETHOXYCAPRYLYLSILANE; WATER; GINGER; MEDIUM-CHAIN TRIGLYCERIDES; DIMETHICONE/VINYL DIMETHICONE CROSSPOLYMER (SOFT PARTICLE); .ALPHA.-BISABOLOL, (+/-)-; BUTYLOCTYL SALICYLATE; CAPRYLYL GLYCOL; CERIC OXIDE; SILICON DIOXIDE; SODIUM CHLORIDE; STEARIC ACID; TRIBEHENIN; VINYL DIMETHICONE/METHICONE SILSESQUIOXANE CROSSPOLYMER; 1,2-HEXANEDIOL; DISTEARDIMONIUM HECTORITE; POLY(METHYL METHACRYLATE; 450000 MW); APRICOT KERNEL OIL; .ALPHA.-TOCOPHEROL, DL-; ALPHA-TOCOPHEROL ACETATE; LAURETH-25; LAURETH-3; PHENOXYETHANOL; HIGH DENSITY POLYETHYLENE; CERESIN; DIMETHICONE METHACRYLATE (3000 MW); ALUMINUM OXIDE; RAPESEED STEROL; DIMETHICONE; FERRIC OXIDE RED; POLYHYDROXYSTEARIC ACID (2300 MW); MICA

sunbetter TONE SMART SPF 68 Sunscreen Compact

Drug Facts

Active ingredients

Titanium Dioxide 8.4%

Zinc Oxide 10.0%

Purpose

Sunscreen

Uses

- Helps prevent sunburn.
- If used as directed with other sun protection measures (see Directions), decreases the risk of skin cancer and early skin aging caused by the sun.

Warnings

- For external use only.
- Do not use on damaged or broken skin.
- When using this product keep out of eyes. Rinse with water to remove.
- Stop use and ask a doctor if rash occurs.

Keep out of reach of children. If swallowed, get medical help or contact a Poison Control Center right away.

Directions

- Sun Protection Measures: Spending time in the sun increases your risk of skin cancer and early skin aging. To decrease this risk, regularly use a sunscreen with a Broad Spectrum SPF value of 15 or higher and other sun protection measures including:
- limit time in the sun, especially from 10 a.m. - 2 p.m.
- wear long-sleeved shirts, pants, hats and sunglasses.
- Children under 6 months of age: Ask a doctor.

DOSAGE AND ADMINISTRATION

Apply liberally and evenly 15 minutes before sun exposure.

Reapply:

after 80 minutes of swimming or sweating.

immediately after towel drying.

at least every 2 hours.

use a water resistant sunscreen if swimming or sweating.

Inactive ingredients

1,2-Hexanediol, Acrylates/Dimethicone Copolymer, Alumina, Bis-Vinyl Dimethicone/Dimethicone Copolymer, Bisabolol, Brassica Campestris (Rapeseed) Sterols, Butyloctyl Salicylate, Caprylic/Capric Triglyceride, Caprylyl Glycol, Cerium Oxide, Cetylhydroxyproline Palmitamide, Dimethicone, Dimethicone/Vinyl Dimethicone Crosspolymer, Disteardimonium Hectorite, Ethylhexylglycerin, Hexyldecanol, Himanthalia Elongata Extract, Hydrogenated Vegetable Oil, Iron Oxides (CI 77491, CI 77492, CI 77499), Laureth-25, Laureth-3, Mica, Octyldodecyl Neopentanoate, Ozokerite, Phenethyl Alcohol, Phenoxyethanol, Phenyl Trimethicone, Plankton Extract, Polyethylene, Polyhydroxystearic Acid, Polymethyl Methacrylate, Prunus Armeniaca (Apricot) Kernel Oil, Silica, Simethicone, Sodium Chloride, Stearic Acid, Tocopherol, Tocopheryl Acetate, Tribehenin, Triethoxycaprylylsilane, Vinyl Dimethicone/Methicone Silsesquioxane Crosspolymer, Water, Zingiber Officinale (Ginger) Root Extract.

Other information

- Protect this product from excessive heat and direct sun.

Questions or comments?

800-538-5600

Principal Display Panel

sun better™
Advanced Mineral Protection

BROAD SPECTRUM SPF 68
SUNSCREEN COMPACT

TONE SMART

Water-Resistant (80 Minutes)

Mineral Actives
skinbetter science®
Net wt. 0.42 oz (12g)

Peel Here